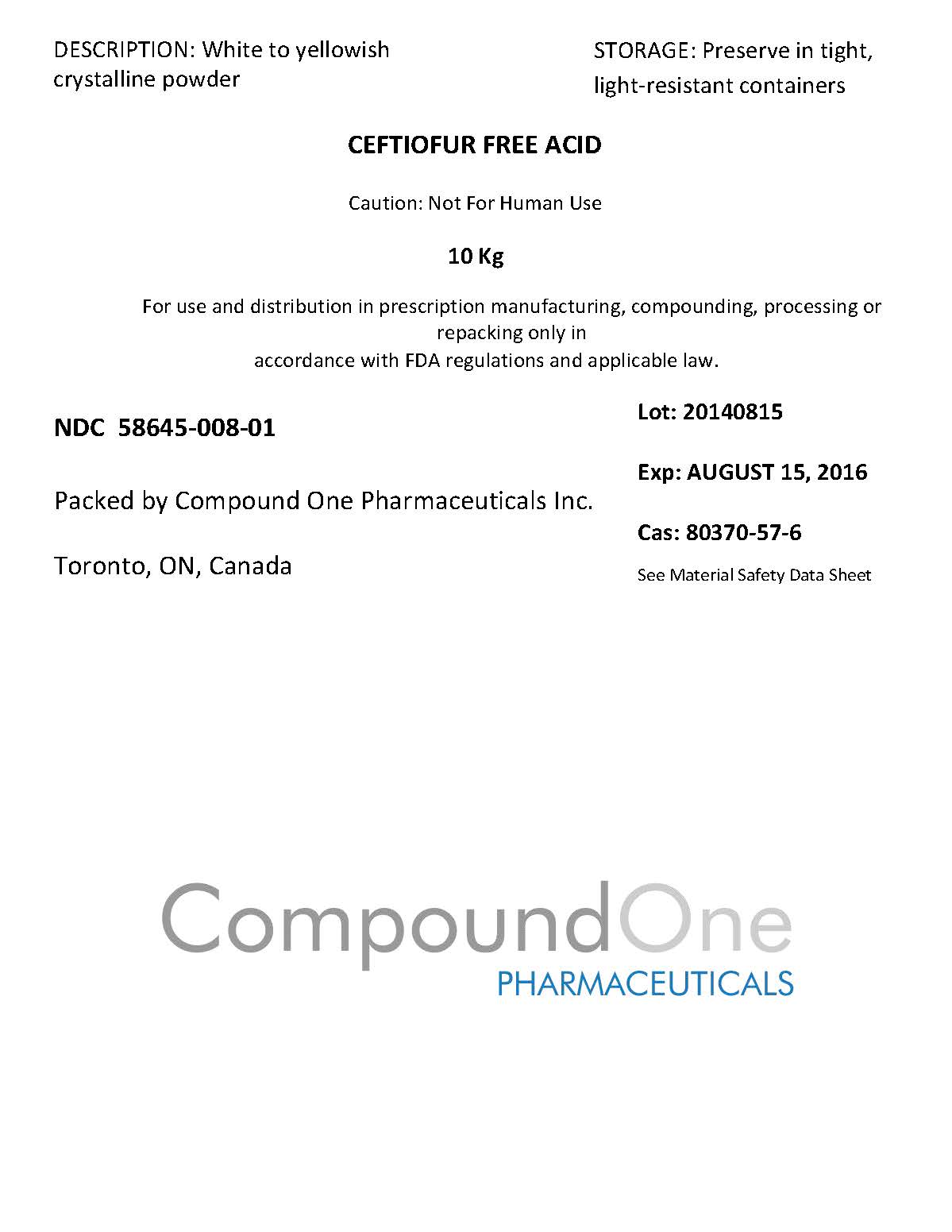 DRUG LABEL: CEFTIOFUR
                
NDC: 58645-008 | Form: POWDER
Manufacturer: Compound One Pharmaceuticals Inc
Category: other | Type: BULK INGREDIENT
Date: 20141119

ACTIVE INGREDIENTS: CEFTIOFUR 1 g/1 g

Drug Facts